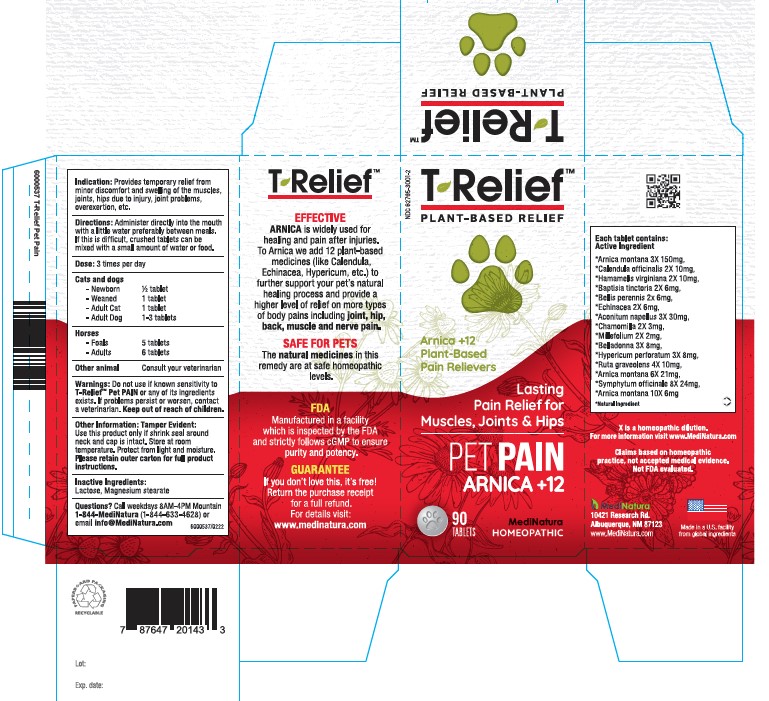 DRUG LABEL: T-Relief Pet Pain
NDC: 62795-3001 | Form: TABLET
Manufacturer: MediNatura New Mexico Inc
Category: homeopathic | Type: OTC ANIMAL DRUG LABEL
Date: 20230510

ACTIVE INGREDIENTS: ARNICA MONTANA 3 [hp_X]/1 1; CALENDULA OFFICINALIS FLOWERING TOP 2 [hp_X]/1 1; HAMAMELIS VIRGINIANA ROOT BARK/STEM BARK 2 [hp_X]/1 1; BAPTISIA TINCTORIA ROOT 2 [hp_X]/1 1; BELLIS PERENNIS 2 [hp_X]/1 1; ECHINACEA ANGUSTIFOLIA 2 [hp_X]/1 1; ACONITUM NAPELLUS 3 [hp_X]/1 1; MATRICARIA CHAMOMILLA 2 [hp_X]/1 1; ACHILLEA MILLEFOLIUM 2 [hp_X]/1 1; ATROPA BELLADONNA 3 [hp_X]/1 1; HYPERICUM PERFORATUM 3 [hp_X]/1 1; RUTA GRAVEOLENS FLOWERING TOP 4 [hp_X]/1 1; COMFREY ROOT 8 [hp_X]/1 1
INACTIVE INGREDIENTS: MAGNESIUM STEARATE; LACTOSE MONOHYDRATE

T-Relief Pet Pain

WARNINGS

Do not use if known sensitivity to T-Relief Pet Pain or any of its ingredients exists.
If problems persist or worsen, contact a veterinarian.

Indications

Provides temporary relief from minor discomfort and swelling of the muscles, joints, hips due to injury, joint problems, over exertion, etc.

DIRECTIONS

Administer directly into the mouth with a little water preferably between meals. If this is difficult, crushed tablets can be mixed with small amount of water or food.
Dose: 3 times per day
Cats and Dogs
-Newborn - ½ tablet
Weaned- 1 tablet
Adult Cat -1 tablet
Adult Dog -1-3 tablets
Horses
Foals – 5 tablets
Adults – 6 tablets
Other animals consult your veterinarian

INACTIVE INGREDIENTS

Lactose, Magnesium Stearate

KEEP OUT OF REACH OF CHILDREN

USES

Provides temporary relief of minor joint pain and stiffness, and mild impaired mobility such as limping.

Active Ingredients:

Each tablet contains: ARNICA MONTANA 3X 150 mg. Calendula officinalis 2X 10mg., HAMAMELIS VIRGINIANA 2X 10mg. BAPTISIA TINCTORIA 2X 6mg. BELLIS PERENNIS 2X 6mg. ECHINACEA ANGUSTIFOLIA 2X 6mg. ACONITUM NAPELLUS 3 X 30mg., Chamomilla 2 X 3mg. MILLEFOLIUM 2 X 2mg. BELLADONNA 3 X 8mg. HYPERICUM PERFORATUM 3 X 8mg. RUTA GRAVEOLENS 4 X 10mg. ARNICA MONTANA 6 X 21mg. Symphytum officinale 8 X 24mg. ARNICA MONTANA 10 X 6mg.
*Natural Ingredients

PACKAGE LABEL

Add image transcription here...